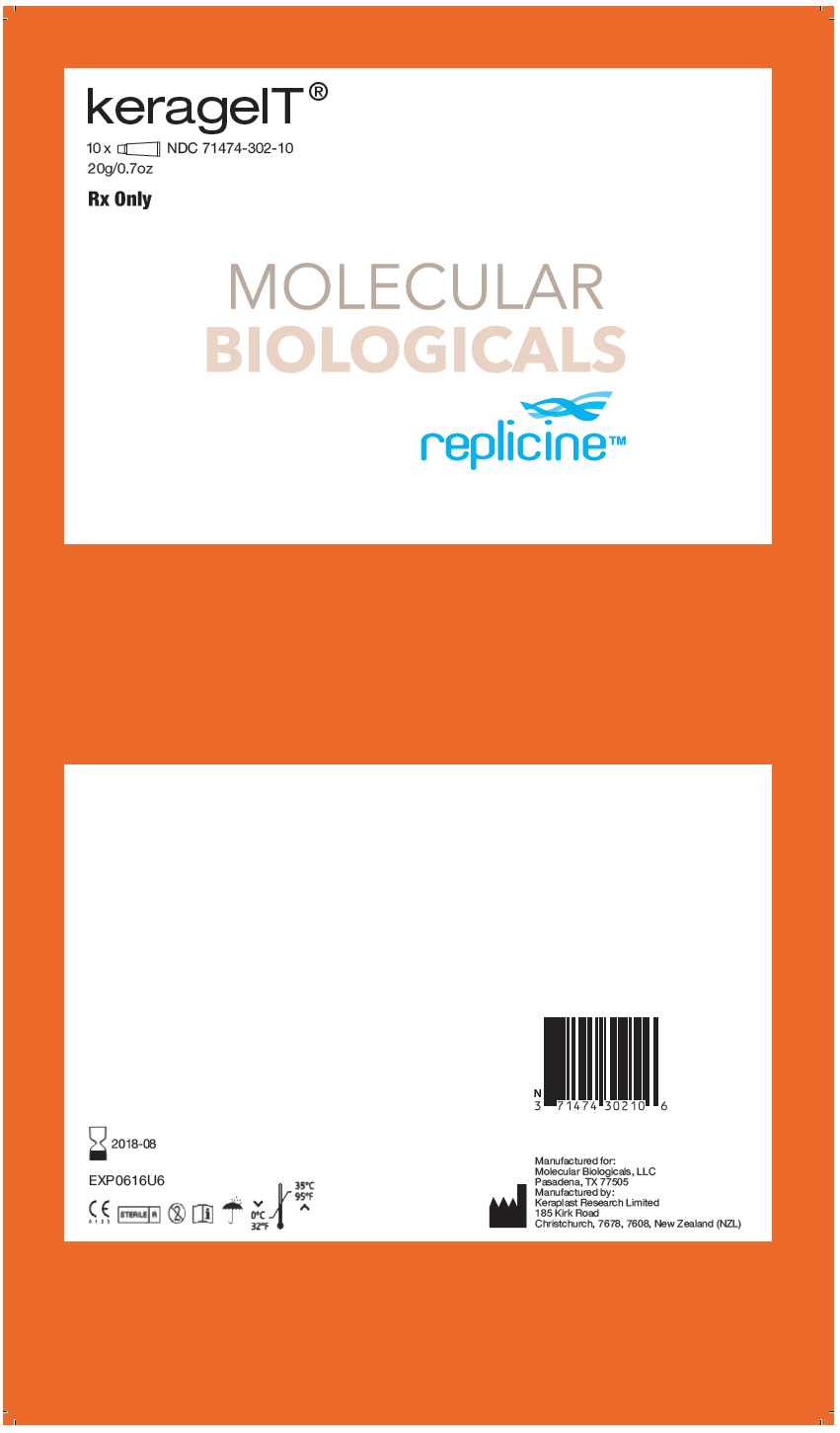 DRUG LABEL: keragelT
NDC: 71474-302
Manufacturer: MOLECULAR BIOLOGICALS, LLC
Category: other | Type: PRESCRIPTION MEDICAL DEVICE LABEL
Date: 20181008

ACTIVE INGREDIENTS: Glycerin 100 mg/1 g

keragelT®
Wound Gel

Rx Only
Single Use
For Topical Dermatological use only.

STERILE | R

C E
0 1 2 3

Description

keragelT® is a keratin enriched gel category dressing utilizing keratin technology to create and maintain a moist wound environment. It is presented sterile in a tube for ease of application.

INDICATIONS FOR USE

keragelT® is designed for acute/chronic superficial and partial thickness wounds with dry to medium exudate, such as:

- Venous leg ulcers
- Arterial ulcers
- Diabetic foot ulcers
- Pressure ulcers
- Skin graft donor sites
- Sunburns
- First and Second Degree burns

ATTENTION

If the wound is infected, it is advised that you consult with your physician or health care professional.

DIRECTIONS FOR USE

1. Cleanse and debride the wound in accordance with normal procedures.
2. Ensure that the skin surrounding the wound is dry.
3. The tube is opened using the piercer cap to break the nozzle seal.
  To ensure sterility, sanitise the piercer cap before using.
4. Apply a 3mm to 6mm (1/8inch to 1/4inch) layer of keragelT® to cover the entire wound surface daily or three times a day as indicated by a healthcare professional.
5. Cover with an appropriate secondary dressing if needed.

RECOMMENDED CARE

The wound should be inspected daily or as indicated by a physician. For wounds that appear dry more gel should be applied to the area.

INGREDIENTS

Keratin, phenoxyethanol, hydroxyethylcellulose, glycerol, sorbitol, propylene glycol, lactic acid.

HOW SUPPLIED

keragelT® 20gm individual tube: | NDC 71474-302-20
keragelT® 5gm individual tube: | NDC 71474-302-05

STORAGE / PRECAUTIONS

keragelT® should be stored in dry conditions between 0° and 35°C (32° and 95° F).

Do not use if the tube has been damaged prior to use.

Sterility is guaranteed until the tube is first opened.

Do not re-sterilise.

CAUTION: RX ONLY. Federal law restricts this device to sale by or on the order of a physician.

Manufactured for: Molecular Biologicals, LLC
Pasadena, TX 77505 | 1-844-793-9933

EC | REP

Keraplast Research Limited, Gerald St., Lincoln 7674, NZ
Medical Device Consultancy, 7 Pinewood Drive, Ashley Heath,
Market Drayton, Shropshire TF9 4PA, United Kingdom

keragelT® is a registered trademark of
Keraplast Technologies LLC.
The product incorporates patented and/or patent pending
technologies owned by Keraplast Technologies LLC.

Issue Date 9/2017
DWG107/1

PRINCIPAL DISPLAY PANEL - 20 g Tube Box

keragelT®

10 x
NDC 71474-302-10
20g/0.7oz

Rx Only

MOLECULAR
BIOLOGICALS

replicine™